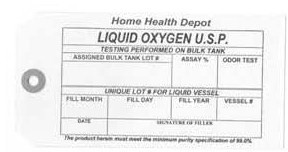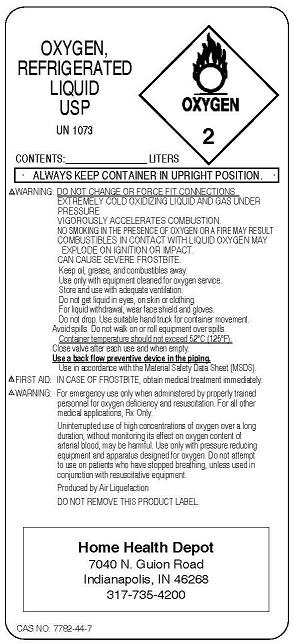 DRUG LABEL: Oxygen
NDC: 50191-0001 | Form: GAS
Manufacturer: Home Health Depot
Category: prescription | Type: HUMAN PRESCRIPTION DRUG LABEL
Date: 20091218

ACTIVE INGREDIENTS: Oxygen 99 L/100 L

Oxygen